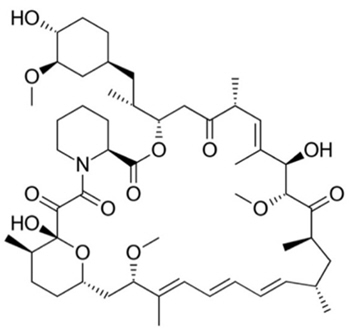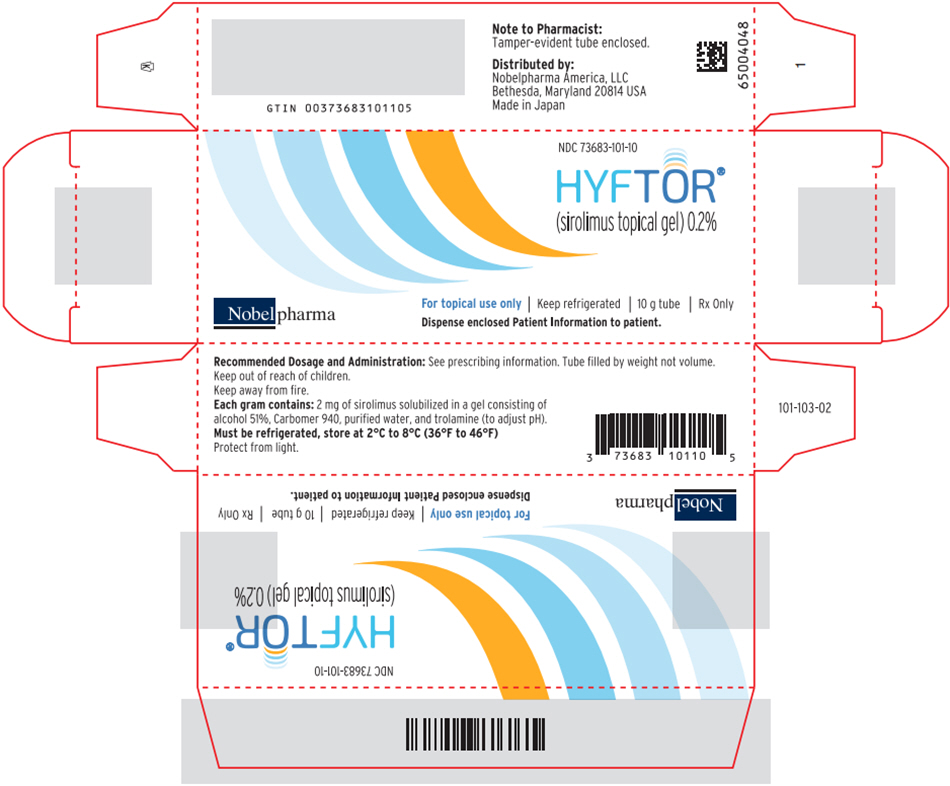 DRUG LABEL: HYFTOR
NDC: 73683-101 | Form: GEL
Manufacturer: Nobelpharma America, LLC
Category: prescription | Type: HUMAN PRESCRIPTION DRUG LABEL
Date: 20250822

ACTIVE INGREDIENTS: SIROLIMUS 2 mg/1 g
INACTIVE INGREDIENTS: CARBOMER HOMOPOLYMER TYPE C (ALLYL PENTAERYTHRITOL CROSSLINKED); ALCOHOL; TROLAMINE; WATER

HIGHLIGHTS OF PRESCRIBING INFORMATION

These highlights do not include all the information needed to use HYFTOR®safely and effectively. See full prescribing information for HYFTOR.
HYFTOR®(sirolimus topical gel)
Initial U.S. Approval: 1999

1 INDICATIONS AND USAGE

HYFTOR is an mTOR inhibitor immunosuppressant indicated for the treatment of facial angiofibroma associated with tuberous sclerosis in adults and pediatric patients 6 years of age and older. (1)

2 DOSAGE AND ADMINISTRATION

- Complete all age-appropriate vaccinations as recommended by current immunization guidelines prior to HYFTOR initiation. (2)
- Apply to the skin of the face affected with angiofibroma twice daily. (2)
- The maximum daily dosage is:
  - 600 mg (2 cm) for patients 6 to 11 years of age. (2)
  - 800 mg (2.5 cm) for patients 12 years of age and older. (2)
- Do not use with occlusive dressings. (2)
- For topical use only. Not for oral, ophthalmic, or intravaginal use. (2)

3 DOSAGE FORMS AND STRENGTHS

Topical gel, 0.2%:2 mg of sirolimus per gram. (3)

4 CONTRAINDICATIONS

History of hypersensitivity to sirolimus or any other component of HYFTOR. (4)

5 WARNINGS AND PRECAUTIONS

- Hypersensitivity Reactions: Oral sirolimus has been associated with hypersensitivity reactions, including anaphylactic/anaphylactoid reactions, angioedema, exfoliative dermatitis, and hypersensitivity vasculitis. Discontinue HYFTOR immediately if symptoms of hypersensitivity occur. (5.1)
- Serious Infection: Serious infections, including opportunistic infections and latent viral infections, such as progressive multifocal leukoencephalopathy, have been reported with oral sirolimus. Discontinue HYFTOR immediately if symptoms of infection occur. (5.2)
- Malignancy: Oral sirolimus has been associated with malignancy, including lymphoma and skin cancer. Patients should minimize or avoid exposure to natural or artificial sunlight (tanning beds or UVA/B treatment) while using HYFTOR. (5.3)
- Hyperlipidemia: Oral sirolimus has been associated with increased serum cholesterol and triglycerides requiring treatment. Monitor for hyperlipidemia during treatment. (5.4)
- Interstitial Lung Disease (ILD)/Non-infectious Pneumonitis: Oral sirolimus has been associated with ILD, sometimes fatal. Discontinue HYFTOR if ILD symptoms occur. (5.5)
- Immunizations:During treatment with HYFTOR, vaccinations may be less effective. Avoid use of live vaccines during treatment with HYFTOR. (5.6)
- Embryo-Fetal Toxicity: Based on animal studies, HYFTOR can cause fetal harm. Use of effective contraception is recommended for females of reproductive potential prior to and throughout treatment, and for 12 weeks after final dose of HYFTOR. (5.7, 8.1, 8.3)
- Male Infertility: Oral sirolimus has been associated with azoospermia and oligospermia. Advise males that HYFTOR may impair fertility. (5.8, 8.3, 13.1)

6 ADVERSE REACTIONS

Most common adverse reactions (≥1%) are dry skin, application site irritation, pruritus, acne, acneiform dermatitis, ocular hyperemia, skin hemorrhage, and skin irritation. (6)

To report SUSPECTED ADVERSE REACTIONS, contact Nobelpharma America, LLC at 1 (877) 375-0825 or FDA at 1-800-FDA-1088 or www.fda.gov/medwatch.

7 DRUG INTERACTIONS

- CYP3A4 Inhibitors:During concomitant use of HYFTOR with CYP3A4 inhibitors, monitor for adverse reactions of HYFTOR. (7.1)
- Substrates and Inhibitors of CYP3A: During concomitant use of HYFTOR with drugs that are both substrates and inhibitors of CYP3A, monitor for adverse reactions of the CYP3A substrate and inhibitor. (7.2)

8 USE IN SPECIFIC POPULATIONS

Lactation: Breastfeeding not recommended. (8.2)

FULL PRESCRIBING INFORMATION

1 INDICATIONS AND USAGE

HYFTOR is indicated for the treatment of facial angiofibroma associated with tuberous sclerosis in adults and pediatric patients 6 years of age and older.

2 DOSAGE AND ADMINISTRATION

- Complete all age-appropriate vaccinations as recommended by current immunization guidelines prior to HYFTOR initiation [see Warning and Precautions (5.6)] .
- Apply HYFTOR to the skin of the face affected with angiofibroma twice daily in the morning and at bedtime.
- The maximum recommended daily dosage is:
  - 600 mg (2 cm) for pediatric patients 6 to 11 years of age
  - 800 mg (2.5 cm) for adults and pediatric patients 12 years of age and older
- If symptoms do not improve within 12 weeks of treatment, reevaluate the need for continuing HYFTOR.
- Do not use HYFTOR with occlusive dressings.
- For topical use only. Not for oral, ophthalmic, or intravaginal use.

3 DOSAGE FORMS AND STRENGTHS

Topical gel ,0.2%: Each gram contains 2 mg of sirolimus in a colorless and transparent gel in 10-gram tubes.

4 CONTRAINDICATIONS

HYFTOR is contraindicated in patients with a history of hypersensitivity to sirolimus or any other component of HYFTOR. Reactions to sirolimus have included anaphylactic/anaphylactoid reactions, angioedema, exfoliative dermatitis, and hypersensitivity vasculitis [see Warning and Precautions (5.1)] .

5 WARNINGS AND PRECAUTIONS

5.1 Hypersensitivity Reactions

Hypersensitivity reactions, including anaphylactic/anaphylactoid reactions, angioedema, exfoliative dermatitis, and hypersensitivity vasculitis have been associated with the oral administration of sirolimus. The concomitant use of HYFTOR with other drugs known to cause angioedema, such as angiotensin-converting enzyme (ACE) inhibitors, may increase the risk of developing angioedema. Elevated sirolimus levels (with or without concomitant ACE inhibitors) may also potentiate angioedema. Discontinue HYFTOR immediately if symptoms of hypersensitivity occur.

5.2 Serious Infection

Serious infections, including opportunistic infections, have been reported after oral administration of sirolimus. Cases of progressive multifocal leukoencephalopathy (PML), sometimes fatal have been reported in patients treated with oral sirolimus. Discontinue HYFTOR immediately if symptoms of infection occur.

5.3 Malignancy

Lymphoma and other malignancies, particularly of the skin, have been observed after oral administration of sirolimus. Patients should minimize or avoid exposure to natural or artificial sunlight (tanning beds or UVA/B treatment) while using HYFTOR. If patients need to be outdoors while using HYFTOR, they should wear protective clothing and discuss other sun protection measures with their physician.

5.4 Hyperlipidemia

Increased serum cholesterol and triglycerides requiring treatment have been observed with oral administration of sirolimus. Monitor for hyperlipidemia during treatment with HYFTOR.

5.5 Interstitial Lung Disease/Non-Infectious Pneumonitis

Cases of interstitial lung disease [ILD] (including pneumonitis, bronchiolitis obliterans organizing pneumonia [BOOP], and pulmonary fibrosis), some fatal, with no identified infectious etiology have occurred in patients receiving oral sirolimus. In some cases, the ILD has resolved upon discontinuation or dosage reduction of oral sirolimus. Discontinue HYFTOR immediately if symptoms of ILD occur.

5.6 Immunizations

During treatment with HYFTOR, vaccinations may be less effective. Complete all age-appropriate vaccinations as recommended by current immunization guidelines prior to initiating treatment with HYFTOR. The use of live vaccines should be avoided during treatment with HYFTOR.

5.7 Embryo-Fetal Toxicity

Based on animal studies and the mechanism of action, oral sirolimus can cause fetal harm when administered to a pregnant woman. In animal studies, oral sirolimus caused embryo-fetal toxicity when administered during the period of organogenesis at maternal exposures that were equal to or less than human exposures at the recommended lowest starting dose. HYFTOR is systemically absorbed after topical administration and may result in fetal exposure. Advise pregnant women of the potential risk to a fetus. Advise female patients of reproductive potential to avoid becoming pregnant. They should use effective contraception prior to, throughout treatment and for 12 weeks after the final dose of HYFTOR [see Use in Specific Populations (8.1, 8.3), Clinical Pharmacology (12.1, 12.3)].

5.8 Male Infertility

Azoospermia or oligospermia has been observed after oral administration of sirolimus [see Use in Specific Populations (8.3), Nonclinical Toxicology (13.1)]. Sirolimus is an anti-proliferative drug and affects rapidly dividing cells like the germ cells. Advise males that HYFTOR may impair fertility.

6 ADVERSE REACTIONS

6.1 Clinical Trials Experience

Because clinical trials are conducted under widely varying conditions, adverse reaction rates observed in the clinical trials of a drug cannot be directly compared to rates in the clinical trials of another drug and may not reflect the rates observed in practice.

In a randomized, double-blind, vehicle-controlled trial, subjects aged 6 years and older with facial angiofibroma associated with tuberous sclerosis applied HYFTOR twice daily for 12 weeks. A total of 30 subjects were treated with HYFTOR and 32 with the vehicle. The majority of the subjects were female (54.8%). A total of 40.3% were less than 18 years of age.

The most common adverse reactions reported by ≥1% of subjects treated with HYFTOR and more frequently than in subjects treated with vehicle are presented in Table 1. Adverse reactions occurred with similar frequency in pediatric subjects 6 years of age and older.

Table 1: Adverse Reactions in ≥1% of Subjects Aged 6 Years and Older with Facial Angiofibroma Associated with Tuberous Sclerosis Through Week 12
Preferred Term | HYFTOR N = 30 | Vehicle N = 32
Dry skin [Dry skin includes dry skin and asteatosis] | 12 (40%) | 4 (13%)
Application site irritation | 11 (37%) | 9 (28%)
Pruritus | 5 (17%) | 4 (13%)
Acne | 2 (7%) | 0 (0%)
Acneiform dermatitis | 1 (3%) | 0 (0%)
Ocular hyperemia | 1 (3%) | 0 (0%)
Skin hemorrhage | 1 (3%) | 0 (0%)
Skin irritation | 1 (3%) | 0 (0%)

In a 104-week, open-label safety trial, the most common adverse reactions associated with HYFTOR application were application site irritation (31%), dry skin (28%), acne (20%), pruritus (9%), eye irritation (9%), erythema (7%), acneiform dermatitis (6%), contact dermatitis (5%), solar dermatitis (1%), and photosensitivity reaction (1%). Adverse reactions occurred with similar frequency in adult and pediatric subjects 6 years of age and older.

7 DRUG INTERACTIONS

7.1 Effects of Other Drugs on HYFTOR

Table 2 presents clinically significant drug interactions involving drugs that affect HYFTOR.

Table 2: Effects of CYP3A4 Inhibitors on HYFTOR
Clinical Impact | Concomitant use of HYFTOR with inhibitors of CYP3A4 has the potential to increase the systemic exposure of sirolimus and increase the risk of HYFTOR adverse reactions.
Intervention | Monitor for adverse reactions of HYFTOR.

7.2 Effects of HYFTOR on Other Drugs

Systemic exposure of drugs that are both substrates and inhibitors of CYP3A could be increased with coadministration with HYFTOR. Monitor for adverse reactions of such co-administered drugs.

8 USE IN SPECIFIC POPULATIONS

8.1 Pregnancy

Risk Summary

Based on animal studies and mechanism of action, oral sirolimus can cause fetal harm when administered to a pregnant woman. HYFTOR is systemically absorbed after topical administration and may result in fetal exposure. The available data from case reports on HYFTOR use in pregnant women are insufficient to evaluate for a drug-associated risk of major birth defects, miscarriage, or adverse maternal or fetal outcomes. Animal reproduction studies have not been conducted with HYFTOR. In an animal reproduction study, oral administration of 0.5 mg/kg/day sirolimus caused embryo-fetal lethality in pregnant rats when administered during the period of organogenesis (see Data). The available data do not allow the calculation of relevant comparisons between the systemic exposure of sirolimus observed in animal studies to the systemic exposure that would be expected in humans after topical use of HYFTOR.

The background risk of major birth defects and miscarriage for the indicated population is unknown. All pregnancies have a background risk of birth defect, loss, or other adverse outcomes. In the U.S. general population, the estimated background risk of major birth defects and miscarriage in clinically recognized pregnancies is 2 to 4% and 15 to 20%, respectively.

Data

Animal Data

In embryo-fetal development studies in rats, oral administration of sirolimus to pregnant rats during the period of organogenesis (gestation days 6 -15) induced embryo-fetal lethality at 0.5 mg/kg/day, reduced fetal body weight at 1.0 mg/kg/day and caused maternal toxicity at 2.0 mg/kg/day. No treatment related embryo-fetal developmental effects were observed at 0.1 mg/kg/day.

In embryo-fetal development studies in rabbits, oral administration of sirolimus to pregnant rabbits during the period of organogenesis (gestation days 6 -18) induced maternal toxicity (decreased body weight) at 0.05 mg/kg/day, which was associated with embryo-fetal loss or early resorption. No treatment related developmental effects were observed at 0.025 mg/kg/day.

In a pre- and postnatal development toxicity study, oral administration of sirolimus to pregnant rats during gestation and lactation (gestation day 6 through lactation day 20) increased the incidence of dead pups, resulting in reduced live litter size at 0.5 mg/kg/day. No treatment related developmental effects were observed at 0.1 mg/kg/day.

Sirolimus did not cause maternal toxicity or affect developmental parameters in the surviving offspring (morphological development, motor activity, learning, or fertility assessment) at 0.5 mg/kg/day, the highest dose tested.

8.2 Lactation

Risk Summary

There are no available data on the presence of sirolimus in human milk, the effects on the breastfed infant, or the effects on milk production. After oral administration, sirolimus was present in the milk of lactating rats. Because of the potential for serious adverse reactions in the breastfed infant, breastfeeding is not recommended during treatment with HYFTOR.

8.3 Females and Males of Reproductive Potential

Contraception

Based on animal studies with oral sirolimus, HYFTOR may cause fetal harm when administered to pregnant women. Females of reproductive potential are recommended to avoid becoming pregnant and to use an effective contraceptive method. Effective contraception should be initiated before HYFTOR therapy and used throughout treatment and for 12 weeks after the final dose of HYFTOR [see Warnings and Precautions (5.7), Use in Specific Populations (8.1)] .

Infertility

Based on clinical findings and findings in animal studies, male and female fertility may be compromised by the treatment with sirolimus [see Warnings and Precautions (5.8), Nonclinical Toxicology (13.1)]. Ovarian cysts and menstrual disorders (including amenorrhea and menorrhagia) have been reported in females with the use of oral sirolimus. Azoospermia has been reported in males with the use of oral sirolimus and have been reversible upon discontinuation of sirolimus in most cases.

8.4 Pediatric Use

The safety and effectiveness of HYFTOR have been established in pediatric patients aged 6 years and older for the topical treatment of facial angiofibroma associated with tuberous sclerosis. Use of HYFTOR in this age group is supported by data from a randomized, vehicle-controlled, double-blind 12-week trial along with additional efficacy and long-term safety data from a 104-week open label safety trial. A total of 13 pediatric subjects aged 6 years to 17 years received HYFTOR in the Phase 3 clinical trial along with 48 pediatric subjects aged 3 years to 17 years in the 104-week open label safety trial. Adverse reactions occurred with similar frequency in adult and pediatric subjects [see Adverse Reaction (6.1), Clinical Studies (14)].

The safety and effectiveness of HYFTOR for this indication have not been established in pediatric patients less than 6 years of age.

8.5 Geriatric Use

Clinical studies of HYFTOR did not include sufficient numbers of subjects aged 65 years and over to determine whether they respond differently from younger subjects. Other reported clinical experience has not identified differences in responses between the elderly and younger patients.

11 DESCRIPTION

HYFTOR®(sirolimus topical gel) 0.2% is an mTOR inhibitor immunosuppressant for topical use. Each gram contains 2 mg of sirolimus, which is solubilized in a gel consisting of alcohol 51%, Carbomer 940, purified water, and trolamine.

Chemically, sirolimus is designated as (3 S,6 R,7 E,9 R,10 R,12 R,14 S,15 E,17 E,19 E,21 S,23 S,26 R,27 R,34a S)-9,10,12,13,14,21,22,23,24,25,26,27,32,33,34,34a-hexadecahydro-9,27-dihydroxy-3-[(1 R)-2-[(1 S,3 R,4 R)-4-hydroxy-3-methoxycyclohexyl]-1-methylethyl]-10,21-dimethoxy-6,8,12,14,20,26-hexamethyl-23,27-epoxy-3 H-pyrido[2,1- c][1,4]oxaazacyclohentriacontine-1,5,11,28,29(4 H,6 H,31 H)-pentone. It has the following structural formula:

Sirolimus is a white to off-white powder and is insoluble in water, but freely soluble in chloroform, acetone and acetonitrile. Sirolimus has a molecular formula of C51H79NO13and a molecular weight of 914.19.

12 CLINICAL PHARMACOLOGY

12.1 Mechanism of Action

The mechanism of action of sirolimus in the treatment of angiofibroma associated with tuberous sclerosis is unknown. Tuberous sclerosis is associated with genetic defects in TSC1 and TSC2 which leads to the constitutive activation of mammalian target of rapamycin (mTOR). Sirolimus inhibits mTOR activation.

12.3 Pharmacokinetics

Absorption

Following 12 weeks of treatment with HYFTOR in adult and pediatric subjects aged 6 years and older, sirolimus blood concentrations ranged from undetectable to 0.50 ng/mL after multiple doses of HYFTOR in the Phase 3 trial. Periodic blood samples were obtained in the 52-week trial and the maximum sirolimus concentration measured at any time in adult subjects was 3.27 ng/mL and the maximum sirolimus concentration measured at any time in pediatric subjects was 1.80 ng/mL.

Distribution

There was no evidence based on blood concentrations that sirolimus accumulates systemically upon topical application in patients with tuberous sclerosis for periods of up to 1 year.

Elimination

Metabolism

Studies evaluating the metabolism of HYFTOR have not been conducted.

Sirolimus is a substrate for both CYP3A4 and P-gp. Sirolimus is extensively metabolized after oral administration in the intestinal wall and liver and undergoes counter-transport from enterocytes of the small intestine into the gut lumen. Inhibitors of CYP3A4 and P-gp increase sirolimus concentrations. Inducers of CYP3A4 and P-gp decrease sirolimus concentrations. Sirolimus is extensively metabolized by O-demethylation and/or hydroxylation. Seven (7) major metabolites, including hydroxy, demethyl, and hydroxydemethyl, are identifiable in whole blood. Some of these metabolites are also detectable in plasma, fecal, and urine samples. Sirolimus is the major component in human whole blood and contributes to more than 90% of the immunosuppressive activity.

Excretion

Studies evaluating the excretion of HYFTOR have not been conducted.

After a single dose of [^14C] sirolimus oral solution in healthy volunteers, the majority (91%) of radioactivity was recovered from the feces, and only a minor amount (2.2%) was excreted in urine. The mean ± SD terminal elimination half-life (t½) of sirolimus after multiple dosing in stable renal transplant patients was estimated to be about 62 ± 16 hours.

Drug Interaction Studies

Drug interaction studies with HYFTOR have not been conducted. Sirolimus is known to be a substrate for both cytochrome P-450 3A4 (CYP3A4) and p-glycoprotein (P-gp). [see Drug Interactions (7.1, 7.2)] .

13 NONCLINICAL TOXICOLOGY

13.1 Carcinogenesis, Mutagenesis, Impairment of Fertility

Oral carcinogenicity studies were conducted in mice and rats. In an oral carcinogenicity study conducted in female mice, sirolimus administered once daily for 86 weeks was associated with a statistically significant increase in malignant lymphoma at all dose levels compared with control animals. In a second oral mouse carcinogenicity study, sirolimus-related hepatocellular adenoma and carcinoma were induced in male mice. In an oral carcinogenicity study conducted in rats with sirolimus there were no significant findings.

Sirolimus was not genotoxic in the in vitro bacterial reverse mutation assay, the Chinese hamster ovary cell chromosomal aberration assay, the mouse lymphoma cell forward mutation assay, or the in vivo mouse micronucleus assay.

Fertility was decreased in both male and female rats following oral administration of sirolimus 2.0 and 0.5 mg/kg, respectively. In male rats, atrophy of testes, epididymides, prostate, seminiferous tubules and/or reduced sperm counts were observed. In female rats, decreased ovarian and uterine weights and decreased implantation were observed. Testicular tubular degeneration was also seen in a 4-week intravenous study of sirolimus in monkeys at 0.1 mg/kg.

14 CLINICAL STUDIES

A single, randomized, double-blind, vehicle-controlled, multi-center, Phase 3 trial was conducted in Japan to evaluate HYFTOR for the treatment of adults and pediatric patients 6 years of age and older with facial angiofibroma associated with tuberous sclerosis (NCT02635789). A total of 62 Japanese subjects with 3 or more angiofibromas (≥2 mm in diameter with redness in each) on the face were enrolled in this trial. Overall, 28 subjects (45%) were male and 34 (55%) were female. A total of 25 subjects (40%) were between 6 and <18 years of age. In this trial, subjects applied either HYFTOR or vehicle twice daily to the skin of their face affected with angiofibroma for 12 weeks.

The efficacy was assessed by the investigator (live assessment) based on the composite improvement from baseline in size and redness of facial angiofibroma, using subjects' baseline photographs as reference. The proportion of subjects assessed as 'Improved' or 'Markedly Improved' at Week 12 is presented in Table 3. An assessment of 'Improved' was defined as at least a 50% reduction in the size and a 2-level reduction in redness and an assessment of 'Markedly Improved' was defined as at least a 75% reduction in the size and a 3-level reduction in redness.

Table 3: Improvement in Facial Angiofibroma Associated with Tuberous Sclerosis in Patients Aged 6 Years and Older at Week 12
Proportion of Subjects Assessed by the Investigator as: | HYFTOR N=30 | Vehicle N=32
'Improved' or 'Markedly Improved' | 23% | 6%
'Improved' | 13% | 3%
'Markedly Improved' | 10% | 3%

16 HOW SUPPLIED/STORAGE AND HANDLING

How Supplied

HYFTOR®(sirolimus topical gel) 0.2% is a colorless and transparent gel supplied as 10 g in aluminum tubes (NDC 73683-101-10). Each gram contains 2 mg of sirolimus.

Storage and Handling

Store refrigerated at 2° to 8°C (36° to 46°F). Protect from light.

17 PATIENT COUNSELING INFORMATION

Advise the patient to read the FDA-approved patient labeling (Patient Information).

Hypersensitivity

Inform patients that oral sirolimus has been associated with hypersensitivity reactions, including anaphylactic/anaphylactoid reactions, angioedema, exfoliative dermatitis, and hypersensitivity vasculitis. Advise patients to discontinue HYFTOR immediately and seek medical attention if symptoms occur [see Warnings and Precautions (5.1)] .

Serious Infections

Inform patients that oral sirolimus has been associated with increased susceptibility to infections, including opportunistic infections and latent viral infections, such as progressive multifocal leukoencephalopathy (PML). Advise patients to discontinue HYFTOR immediately and seek medical attention if symptoms occur [see Warnings and Precautions (5.2)] .

Malignancy

Inform patients that oral sirolimus has been associated with malignancy, including lymphoma and skin cancer. Advise patients to minimize or avoid exposure to natural or artificial sunlight (tanning beds or UVA/B treatment), and to use protective measures if exposure cannot be avoided, while using HYFTOR [see Warnings and Precautions (5.3)] .

Hyperlipidemia

Inform patients that oral sirolimus has been associated with increased serum cholesterol and triglycerides requiring treatment and that periodic laboratory monitoring may be needed [see Warnings and Precautions (5.4)] .

Interstitial Lung Disease

Inform patients that oral sirolimus has been associated with interstitial lung disease [ILD] sometimes fatal, with no identified infectious etiology. Advise patients to discontinue HYFTOR immediately and seek medical attention if symptoms (e.g. shortness of breath) occur [see Warnings and Precautions (5.5)] .

Immunization

Inform patients that during treatment with HYFTOR, vaccinations may be less effective. Instruct patients that vaccination with live vaccines should be avoided during treatment with HYFTOR and to inform the healthcare practitioner that they are using HYFTOR prior to a potential vaccination [see Warnings and Precautions (5.6)] .

Pregnancy

HYFTOR may cause fetal harm if used during pregnancy. Advise female patients of reproductive potential to avoid becoming pregnant and to use effective contraception prior to, throughout treatment, and for 12 weeks after the final dose of HYFTOR. Advise pregnant women of the potential risk to a fetus [see Warnings and Precautions (5.7), Use in Specific Populations (8.1, 8.3)].

Lactation

Advise lactating women that breastfeeding is not recommended during treatment with HYFTOR [see Use in Specific Populations (8.2)].

Infertility

Inform male and female patients that HYFTOR may impair fertility [see Warnings and Precautions (5.8), Use in Specific Populations (8.3), Nonclinical Toxicology (13.1)].

Administration Information

Inform patients that the skin being treated with HYFTOR should not be covered with bandages, dressings or wraps [see Dosage and Administration (2)].

Distributed by:
Nobelpharma America, LLC
4520 East-West Highway, Suite 400
Bethesda, MD 20814

PATIENT INFORMATION
HYFTOR®(hyfe tore)
(sirolimus topical gel)

Important: HYFTOR is for use on the skin only (topical use).Do not use HYFTOR in your mouth, eyes, or vagina.

What is HYFTOR?
HYFTOR is a prescription medicine that is used on the skin (topical) to treat adults and children 6 years of age and older with a type of noncancerous tumor called angiofibroma on your face caused by the genetic condition tuberous sclerosis.
It is not known if HYFTOR is safe and effective in children under 6 years of age.

Do not use HYFTOR ifyou are allergic to sirolimus or any of the other ingredients in HYFTOR. See the end of this leaflet for a complete list of ingredients in HYFTOR.

Before using HYFTOR, tell your healthcare provider about all of your medical conditions, including if you:

- have a skin infection at the treatment site
- have high cholesterol or high triglycerides (fat or lipids) in your blood
- are scheduled to receive an immunization (vaccine). You should avoid receiving live vaccines during treatment with HYFTOR. Vaccines may be less effective during treatment with HYFTOR.
- are pregnant or plan to become pregnant. HYFTOR may harm your unborn baby. You should not become pregnant during treatment with HYFTOR.
  - Females who are able to become pregnant should use effective birth control (contraception) before starting treatment with HYFTOR, during treatment, and for 12 weeks after your final dose of HYFTOR. Talk to your healthcare provider about types of birth control that you can use during this time.
- are breastfeeding or plan to breastfeed. It is not known if HYFTOR passes into your breast milk. You should not breastfeed during treatment with HYFTOR.

Tell your healthcare provider about all the medicines you take, including prescription and over-the-counter medicines, vitamins, and herbal supplements. Using HYFTOR with certain medicines may affect each other causing side effects.

How should I use HYFTOR?

- Use HYFTOR exactly as your healthcare provider tells you to use it.
- Before you use HYFTOR, your healthcare provider or pharmacist should show you how to correctly measure your dose.
- Wash your hands before and after applying HYFTOR.
- Apply HYFTOR to the skin of the face affected with angiofibroma 2 times a day, in the morning and at bedtime.
- Do notcover, wrap, apply dressings, or bandage the skin area treated with HYFTOR.
- Tell your healthcare provider if the treated skin area does not improve within 12 weeks of treatment.

What should I avoid while using HYFTOR?
Limit your exposure to sunlight and ultraviolet light, such as tanning beds and ultraviolet light therapy, during treatment with HYFTOR. Wear clothing that covers your skin if you need to go outside. Talk with your healthcare provider about other ways you can protect your skin from the sun.

What are the possible side effects of HYFTOR?
HYFTOR may cause serious side effects, including:

- Allergic reactions.Serious allergic reactions have happened in people who have taken sirolimus by mouth. Stop using HYFTOR and get medical help right away if you get any of these symptoms of a serious allergic reaction:

- swelling of your face, eyes, or mouth
- trouble breathing or wheezing
- throat tightness

- chest pain or tightness
- feeling dizzy or faint
- rash or peeling of your skin

- Infections.Serious infections, including infections that can happen when your immune system is weak, have happened in people who have taken sirolimus by mouth. Some people have developed a rare, serious brain infection called progressive multifocal leukoencephalopathy (PML) which can sometimes cause death. Stop using HYFTOR and call your healthcare provider right away if you get symptoms of an infection including fever or chills.
- Risk of cancer.Lymphoma and other cancers, especially skin cancer, have happened in people who have taken sirolimus by mouth. Talk with your healthcare provider about your risk for cancer if you use HYFTOR.
- Increased levels of cholesterol and triglycerides (fat or lipids) in the bloodhave happened in people who have taken sirolimus by mouth .Your healthcare provider may do blood tests to check you for high lipid levels during treatment with HYFTOR and treat you, if needed.
- Lung or breathing problems.Lung or breathing problems, including problems that have sometimes caused death, have happened in people who have taken sirolimus by mouth. Stop using HYFTOR and get medical help right away if you get symptoms such as shortness of breath, new or worsening cough, or chest pain.

The most common side effects of HYFTOR includedry skin, application site irritation, itching, acne, acne-like rash, eye redness, skin bleeding, and skin irritation.
HYFTOR may cause fertility problems in males and females, which may affect your ability to have children. Talk to your healthcare provider if this is a concern for you.
These are not all the possible side effects of HYFTOR.
Call your doctor for medical advice about side effects. You may report side effects to FDA at 1-800-FDA-1088.

How should I store HYFTOR ?

- Store HYFTOR in the refrigerator between at 36°F to 46°F (2°C to 8°C).
- Keep HYFTOR out of light.

Keep HYFTOR and all medicines out of the reach of children.

General information about the safe and effective use of HYFTOR.
Medicines are sometimes prescribed for purposes other than those listed in a Patient Information leaflet. Do not use HYFTOR for a condition for which it was not prescribed. Do not give HYFTOR to other people, even if they have the same symptoms you have. It may harm them. You can ask your pharmacist or healthcare provider for information about HYFTOR that is written for health professionals.

What are the ingredients in HYFTOR?
Active ingredient: sirolimus
Inactive ingredients:alcohol 51%, Carbomer 940, purified water, and trolamine.
Distributed by: Nobelpharma America, LLC
4520 East-West Highway, Suite 400, Bethesda, MD 20814
For more information, go to www.Hyftor.com or call 887-375-0825.

This Patient Information has been approved by the U.S. Food and Drug Administration.

101-104-02
Issued: 5/2025

PRINCIPAL DISPLAY PANEL - 10 g Tube Carton

NDC 73683-101-10

HYFTOR®
(sirolimus topical gel) 0.2%

Nobel pharma

For topical use only | Keep refrigerated | 10 g tube | Rx Only

Dispense enclosed Patient Information to patient.